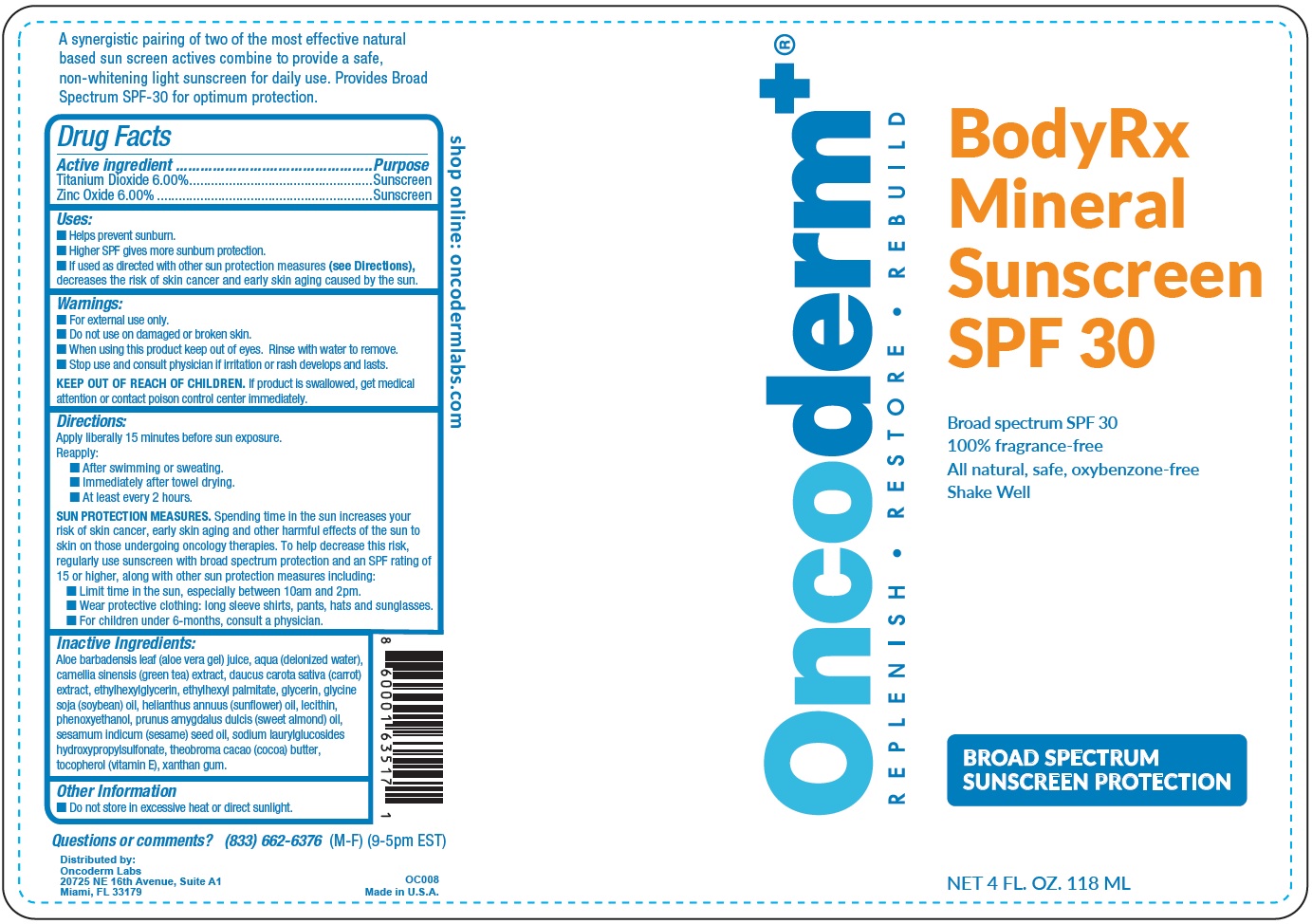 DRUG LABEL: ONCODERM Rx Mineral Sunscreen SPF-30
NDC: 75087-074 | Form: CREAM
Manufacturer: Oncoderm, LLC
Category: otc | Type: HUMAN OTC DRUG LABEL
Date: 20231111

ACTIVE INGREDIENTS: TITANIUM DIOXIDE 60 mg/1 mL; ZINC OXIDE 60 mg/1 mL
INACTIVE INGREDIENTS: ALOE VERA LEAF; WATER; GREEN TEA LEAF; CARROT; ETHYLHEXYLGLYCERIN; ETHYLHEXYL PALMITATE; GLYCERIN; SOYBEAN OIL; SUNFLOWER OIL; PHENOXYETHANOL; ALMOND OIL; SESAME OIL; COCOA BUTTER; .ALPHA.-TOCOPHEROL; XANTHAN GUM

ONCODERM Rx Mineral Sunscreen SPF-30

Active Ingredient

Titanium Dioxide 6.00%

Zinc Oxide 6.00%

Purpose

Sunscreen

Uses:

• Helps prevent sunburn

• Higher SPF gives more sunburn protection

• If used as directed with other sun protection measures (), decreases the risk of skin cancer and early skin aging caused by the sun. see Directions

Warnings:

- For external use only.

• Do not use on damaged or broken skin.

- When using this product keep out of eyes. Rinse with water to remove.

- Stop use and consult physician if irritation or rash develops and lasts.

KEEP OUT OF REACH OF CHILDREN.

If product is swallowed, get medical attention or contact poison control center immediately.

Directions:

Apply liberally 15-minutes before sun exposure. Reapply: ■ After swimming or sweating. ■ Immediately after towel drying. ■ At least every 2 hours.

Spending time in the sun increases your risk of skin cancer, early skin aging and other harmful effects of the sun to skin on those undergoing oncology therapies. To help decrease this risk, regularly use sunscreen with broad spectrum protection and an SPF rating of 15 or higher, along with other sun protection measures including: ■ Limit time in the sun, especially between 10am and 2pm. ■ Wear protective clothing: long sleeve shirts, pants, hats and sunglasses. ■ For children under 6-months, consult a physician. SUN PROTECTION MEASURES.

Inactive Ingredients:

Aloe barbadensis leaf (aloe vera gel) juice, aqua (deionized water), camellia sinensis (green tea) extract, daucus carota sativa (carrot) extract, ethylhexylglycerin, ethylhexyl palmitate, glycerin, glycine soja (soybean) oil, helianthus annuus (sunflower) oil, lecithin, phenoxyethanol, prunus amygdalus dulcis (sweet almond) oil, sesamum indicum (sesame) seed oil, sodium laurylglucosides hydroxypropylsulfonate, theobroma cacao (cocoa) butter, tocopherol (vitamin E), xanthan gum.

Other Information

■ Do not store in excessive heat or direct sunlight.

Questions or comments? (833) 662-6376 (M-F) (9-5pm EST)